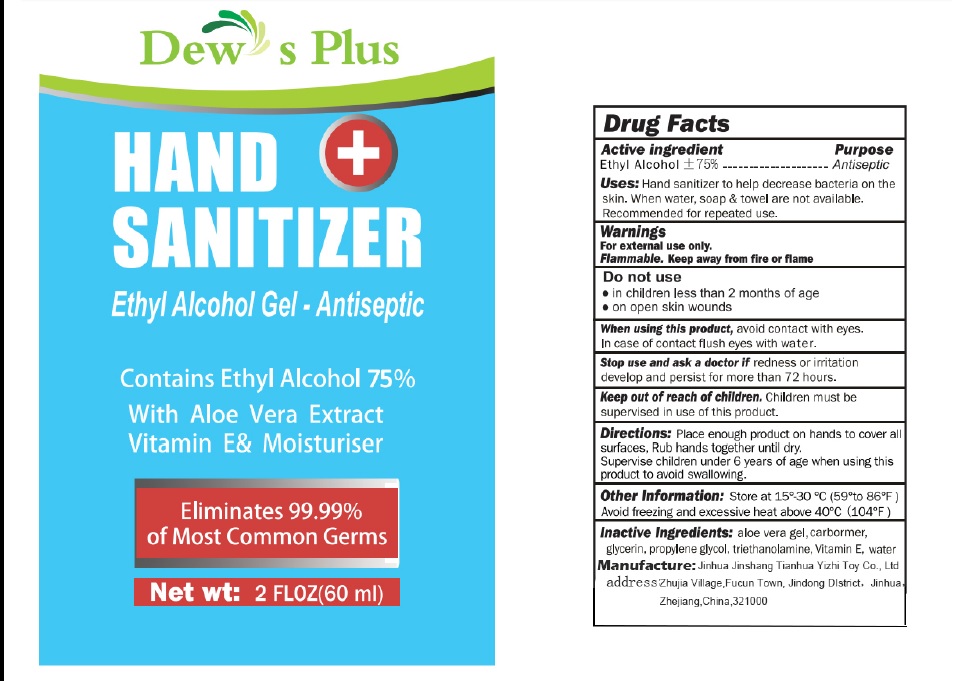 DRUG LABEL: Dews Plus Hand sanitizer
NDC: 41315-002 | Form: GEL
Manufacturer: Jinhua Jinshang Tianhua Yizhi Toy Co., Ltd
Category: otc | Type: HUMAN OTC DRUG LABEL
Date: 20200507

ACTIVE INGREDIENTS: ALCOHOL 75 mL/100 mL
INACTIVE INGREDIENTS: ALOE VERA LEAF; CARBOMER HOMOPOLYMER, UNSPECIFIED TYPE; GLYCERIN; PROPYLENE GLYCOL; TROLAMINE; .ALPHA.-TOCOPHEROL; WATER

Active Ingredient

Ethyl Alcohol 75% v/v.

Purpose

Antiseptic

Uses

Hand Sanitizer to help decrease bacteria on the skin.

When water, soap and towel are not available.

Recommended for repeated use.

Warnings

For external use only. Flammable. Keep away from fire or flame.

Do not use

in children less than 2 months of age

on open skin wounds.

When using this product avoid contact with eyes. In case of contact flush eyes with water.

Stop use and ask a doctor if redness or irritation develop and persist for more than 72 hours.

Keep out of reach of children. Children must be superwised in use of of this product.

Directions

- Place enough product on hands to cover all surfaces. Rub hands together until dry.
- Supervise children under 6 years of age when using this product to avoid swallowing.

Other information

- Store between 15°-30°C (59°-86°F)
- Avoid freezing and excessive heat above 40°C (104°F)

Inactive ingredients

aloe vera gel, carbomer, glycerin, propylene glycol, triethanolamine, Vitamin E, water